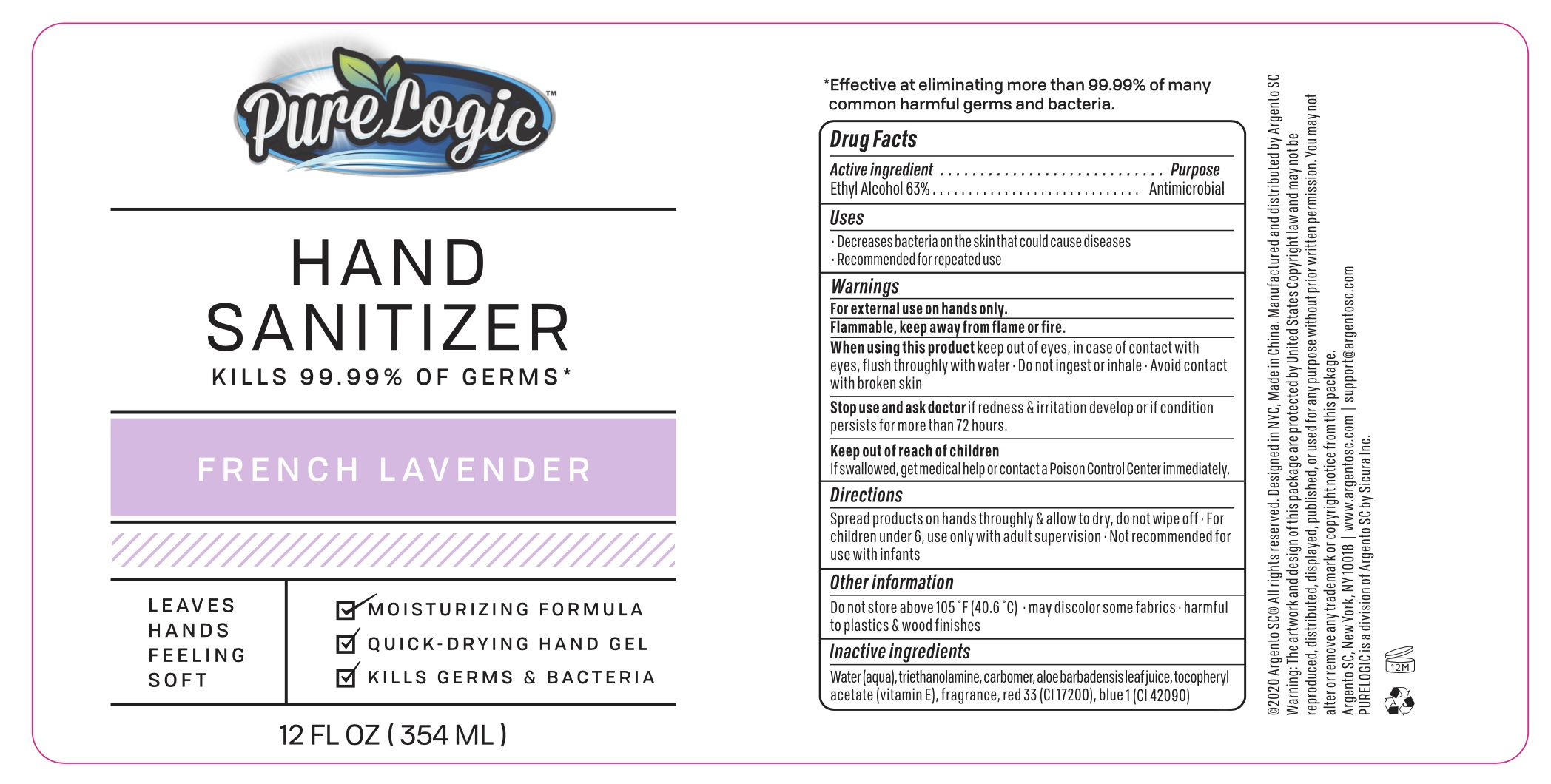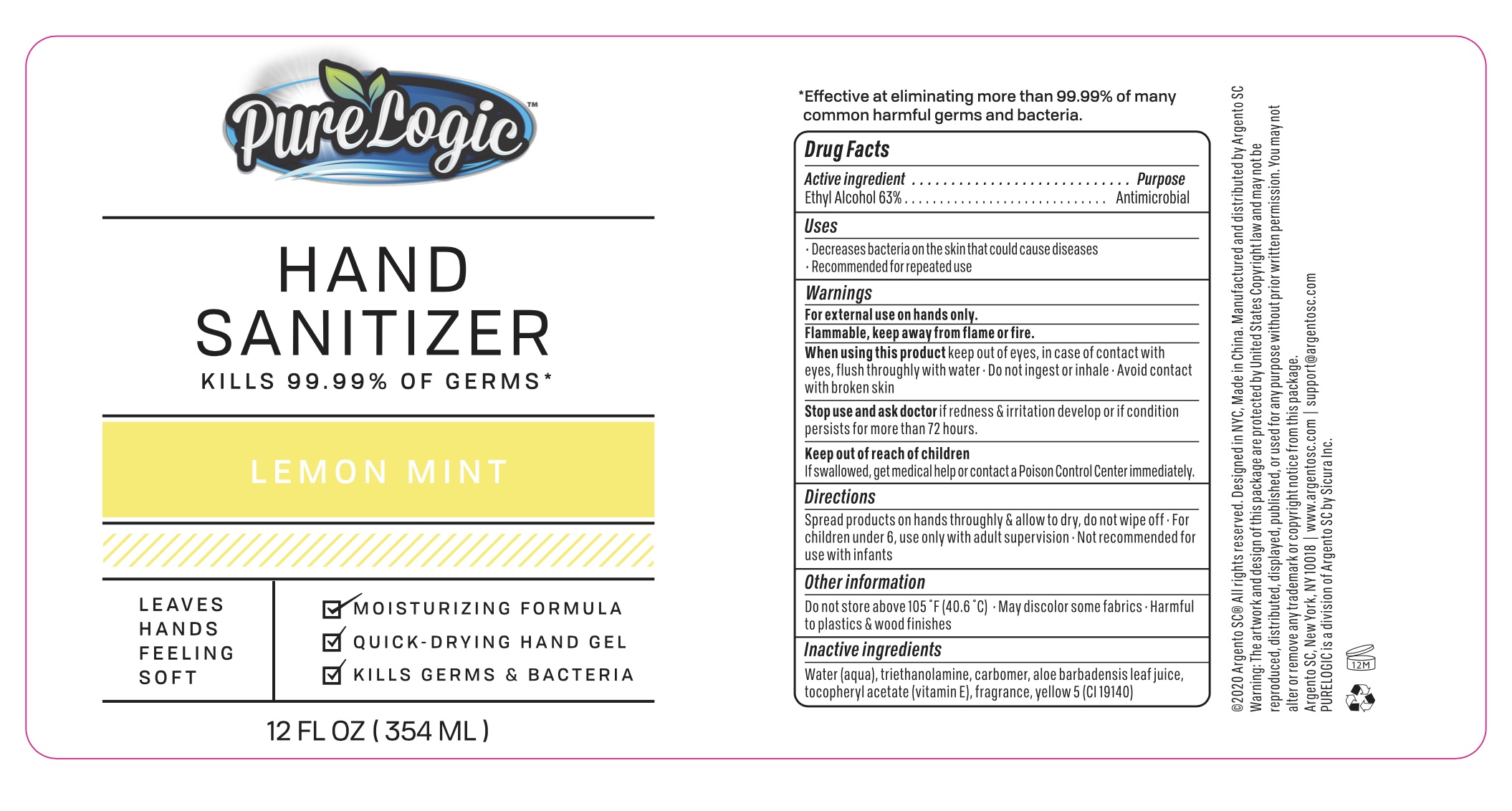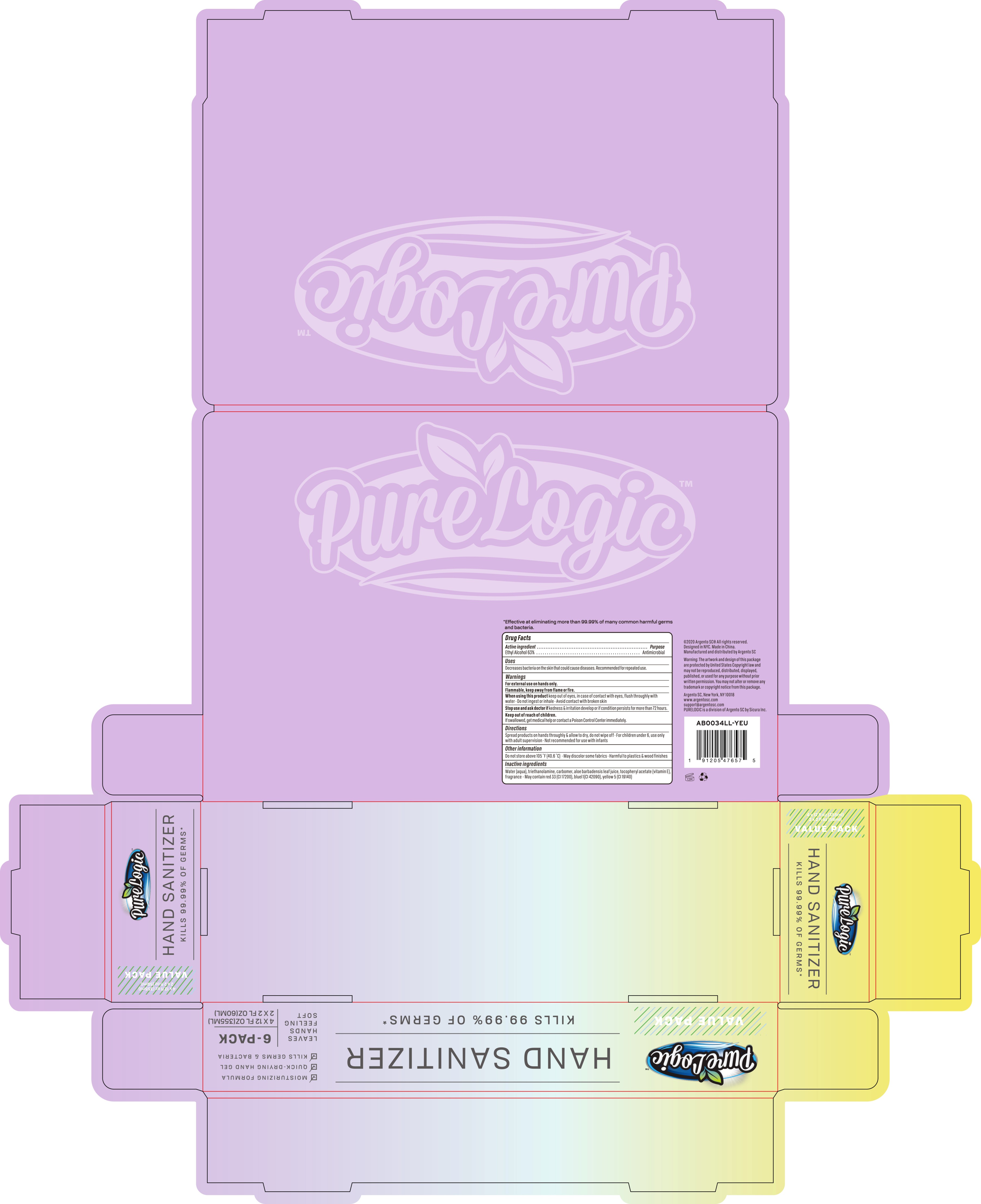 DRUG LABEL: PureLogic Hand Sanitizer French Lavender and Lemon Mint 6 Pack
NDC: 77731-048 | Form: KIT | Route: TOPICAL
Manufacturer: Argento sc by sicura inc.
Category: otc | Type: HUMAN OTC DRUG LABEL
Date: 20200801

ACTIVE INGREDIENTS: ALCOHOL 63 mL/100 mL; ALCOHOL 63 mL/100 mL
INACTIVE INGREDIENTS: WATER; ALOE VERA LEAF; CARBOMER 940; TROLAMINE; .ALPHA.-TOCOPHEROL ACETATE; D&C RED NO. 33; FD&C BLUE NO. 1; WATER; ALOE VERA LEAF; CARBOMER 940; TROLAMINE; .ALPHA.-TOCOPHEROL ACETATE; FD&C YELLOW NO. 5

AB0034LL YUE Kit

PureLogic Hand Sanitizer French Lavender

Active Ingredient

Ethyl Alcohol 63%

Purpose

Antimicrobial

Use

■ Decrease bacteria on the skin that could cause diseases
■Recommended for repeated use

WARNINGS

For external use only, Hands

Flammable. Keep away from flame or fire

When using this product, keep out of eyes.
In case of contact with eyes, flush thoroughly with water

Avoid contact with broken skin

Do not inhale or ingest

Stop Use

Stop use and ask a doctor if redness and irritation develop or if condition persistes for more than 72 hours

Keep out of reach of children. If swalowed, get medical help or contact a poison control center immediately

Directions

Spread product on hands thoroughly and allow to dry, do not wipe off
For children under 6, use under adult supervision
Not recommended for use with infants

Other information

Do not store above 105F (40.6C)

May discolor some fabrics

Harmful to plastics and wood finishes

Inactive ingredients

Purified water, Carbomer, Triethanolamine, Aloe Barbadensis Leaf Juice, Tocopheryl Acetate (Vitamin E), Fragrance, Red 33 (CI17200), Blue 1 (CI42090)

PureLogic Hand Sanitizer Lemon Mint

Active Ingredient

Ethyl Alcohol 63%

Purpose:

Antimicrobial

Uses:

Decrease bacteria on the skin that could cause diseases
■Recommended for repeated use

Warnings

For external use on hands only

Flammable. Keep away from flame or fire

When using this product, keep out of eyes.
In case of contact with eyes, flush thoroughly with water

Avoid contact with broken skin

Do not inhale or ingest

Stop Use

Stop use and ask a doctor if redness and irritation develop or if condition persistes for more than 72 hours

Keep out of reach of children. If swalowed, get medical help or contact a poison control center immediately

Directions

Spread product on hands thoroughly and allow to dry, do not wipe off
For children under 6, use under adult supervision
Not recommended for use with infants

Other Information

Do not store above 105F (40.6C)

May discolor some fabrics

Harmful to wood finishes and plastics

Inactive Ingredients

Purified water, Carbomer, Triethanolamine, Aloe Barbadensis Leaf Juice, Tocopheryl Acetate (Vitamin E), Fragrance, Yellow 5 (CI19140)